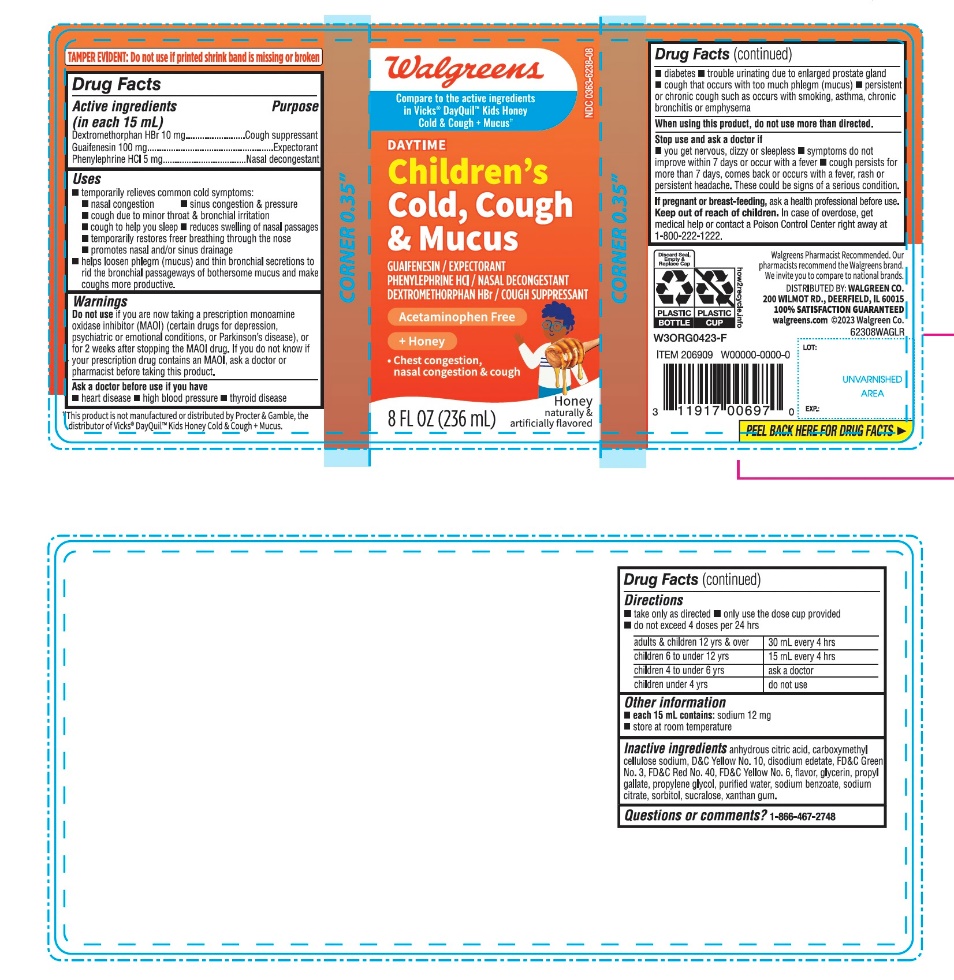 DRUG LABEL: Walgreen Daytimel Kids

NDC: 0363-6238 | Form: LIQUID
Manufacturer: WALGREENS CO.
Category: otc | Type: HUMAN OTC DRUG LABEL
Date: 20251126

ACTIVE INGREDIENTS: DEXTROMETHORPHAN HYDROBROMIDE 10 mg/15 mL; GUAIFENESIN 100 mg/15 mL; PHENYLEPHRINE HYDROCHLORIDE 5 mg/15 mL
INACTIVE INGREDIENTS: ANHYDROUS CITRIC ACID; CARBOXYMETHYLCELLULOSE SODIUM, UNSPECIFIED; D&C YELLOW NO. 10; EDETATE DISODIUM; FD&C GREEN NO. 3; FD&C RED NO. 40; FD&C YELLOW NO. 6; GLYCERIN; PROPYL GALLATE; PROPYLENE GLYCOL; WATER; SODIUM BENZOATE; SODIUM CITRATE, UNSPECIFIED FORM; SORBITOL; SUCRALOSE; XANTHAN GUM

Walgreens Daytime Kids Cold & Cough + Mucus

Drug Facts

Active ingredients (in each 15 mL)

Dextromethorphan HBr 10 mg
Guaifenesin 100 mg

Phenylephrine HCl 5 mg

Purpose

Cough suppressant
Expectorant

Nasal decongestant

Uses

- temporarily relieves common cold symptoms:
- nasal congestion
- sinus congestion & pressure
- cough due to minor throat & bronchial irritation
- cough to help you sleep
- reduces swelling of nasal passages
- temporarily restores freer breathing through the nose
- promotes nasal and/or sinus drainage
- helps loosen phlegm (mucus) and thin bronchial secretions to rid the bronchial passageways of bothersome mucus and make coughs more productive..

Warnings

Do not use

if you are now taking a prescription monoamine oxidase inhibitor (MAOI) (certain drugs for depression, psychiatric or emotional conditions, or Parkinson's disease), or for 2 weeks after stopping the MAOI drug. If you do not know if your prescription drug contains an MAOI, ask a doctor or pharmacist before taking this product.

Ask a doctor before use if you have

- heart disease
- high blood pressure
- thyroid disease
- diabetes
- trouble urinating due to enlarged prostate gland
- cough that occurs with too much phlegm (mucus)
- persistent or chronic cough such as occurs with smoking, asthma, chronic bronchitis or emphysema

When using this product, do not use more than directed.

Stop use and ask a doctor if

- you get nervous, dizzy or sleepless
- symptoms do not improve within 7 days or occur with a fever
- cough persists for more than 7 days, comes back or occurs with a fever, rash or persistent headache

These could be signs of a serious condition.

PREGNANCY OR BREAST FEEDING

If pregnant or breast-feeding, ask a health professional before use.

Keep out of reach of children.

Overdose warning

In case of overdose, get medical help or contact a Poison Control Center right away at 1-800-222-1222.

Directions

- take only as directed
- use dose cup provided
- do not exceed 4 doses per 24 hrs

adults & children 12 yrs & over 30 mL every 4 hrs

children 6 to under 12 yrs 15 mL every 4 hrs
children 4 to under 6 yrs ask a doctor
children under 4 yrs do not use

Other information

- each 15 mL contains:sodium 12 mg
- store at room temperature

Inactive ingredients

citric acid, carboxymethyl cellulose sodium, D&C Yellow No. 10, disodium edetate, FD&C Green No. 3, FD&C Red No. 40, FD&C Yellow No. 6, flavor, glycerin, propyl gallate, propylene glycol, purified water, sodium benzoate, sodium citrate, sorbitol, sucralose, xanthan gum

Questions?

1-866-467-2748

Distributed by:

PRINCIPAL DISPLAY PANEL - 236 ml Bottle Label

Compare to the active ingredients in Kids Vicks ® DayQuil™ Honey Cold & Cough + Mucus

NDC 0363-6238-08

Daytime

Kid’s

Cold & Cough + Mucus

Guaifenesin, Phenylephrine HCl, Dextromethorphan HBr

- Chest Congestion
- Nasal Congestion
- Cough

No Added Alcohol & Acetaminophen free

Honey Flavor

Naturally and Artificially Flavored

8 FL OZ (236 mL)

*This product is not manufactured or distributed by Procter & Gamble, the distributor of Kids Vicks ® DayQuil™ Honey Cold & Cough + Mucus.